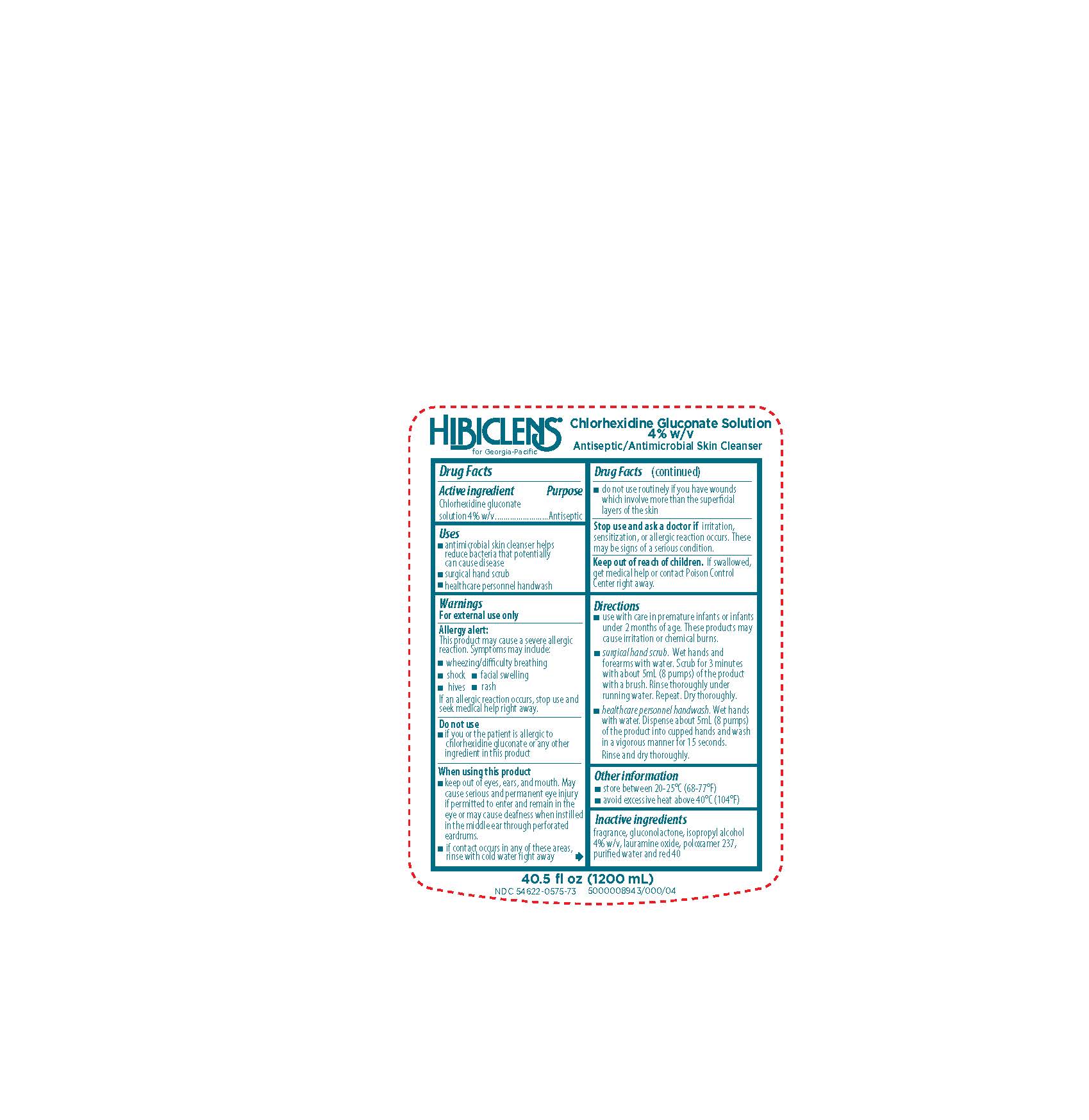 DRUG LABEL: Hibiclens for Georgia Pacific
NDC: 54622-575 | Form: SOLUTION
Manufacturer: Georgia-Pacific Consumer Products LP
Category: otc | Type: HUMAN OTC DRUG LABEL
Date: 20221215

ACTIVE INGREDIENTS: CHLORHEXIDINE GLUCONATE 4 g/100 mL
INACTIVE INGREDIENTS: LAURAMINE OXIDE; GLUCONOLACTONE; FD&C RED NO. 40; WATER; POLOXAMER 237; ISOPROPYL ALCOHOL

Hibiclens for Georgia Pacific

ACTIVE INGREDIENT

Chlorhexidine gluconate solution 4% w/v

PURPOSE

Antiseptic

Uses

- antimicrobial skin cleanser helps reduce bacteria that potentially can cause disease
- surgical hand scrub
- healthcare personnel handwash

Warnings

For external use only

Allergy alert:

This product may cause a severe allergic reaction. Symptoms may include:

- wheezing/difficulty breathing
- shock
- facial swelling
- hives
- rash

If an allergic reaction occurs, stop use and seek medical help right away.

Do not use

- If you or the patient is allergic to chlorhexidine gluconate or any other ingredient in this product

When using this product

- keep out of eyes, ears, and mouth. May cause serious and permanent eye injury if permitted to enter and remain in the eye or may cause deafness when instilled in the middle ear through perforated eardrums.
- if contact occurs in any of these areas, rinse with cold water right away
- do not use routinely if you have wounds which involve more than the superficial layers of the skin

Stop use and ask a doctor if

irritation, sensitization, or allergic reaction occurs. These may be signs of a serious condition.

Keep out of reach of children.

If swallowed, get medical help or contact Poison Control Center right away.

Directions

- use with care in premature infants or infants under 2 months of age. These products may cause irritation or chemical burns.
- surgical hand scrub. Wet hands and forearms with water. Scrub for 3 minutes with about 5mL (8 pumps) of the product with a brush. Rinse thoroughly under running water. Repeat. Dry thoroughly.
- healthcare personnel handwash. Wet hands with water. Dispense about 5mL (8 pumps) of the product into cupped hands and wash in a vigorous manner for 15 seconds. Rinse and dry thoroughly.

Other information

- store between 20-25°C (68-77°F)
- avoid excessive heat above 40°C (104°F)

Inactive ingredients

fragrance, gluconalactone, isopropyl alcohol 4% w/v, lauramine oxide, poloxamer 237, purified water and red 40